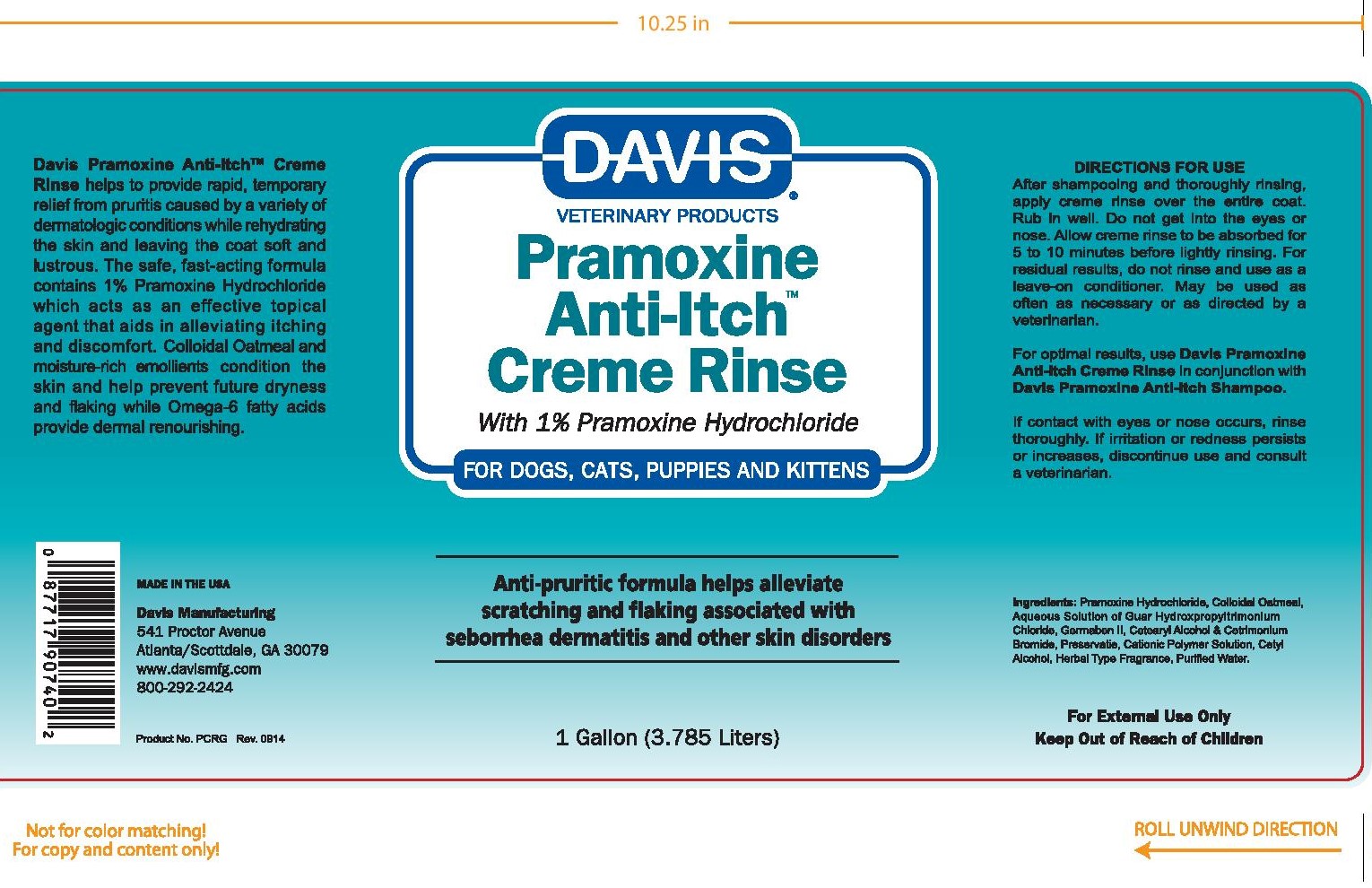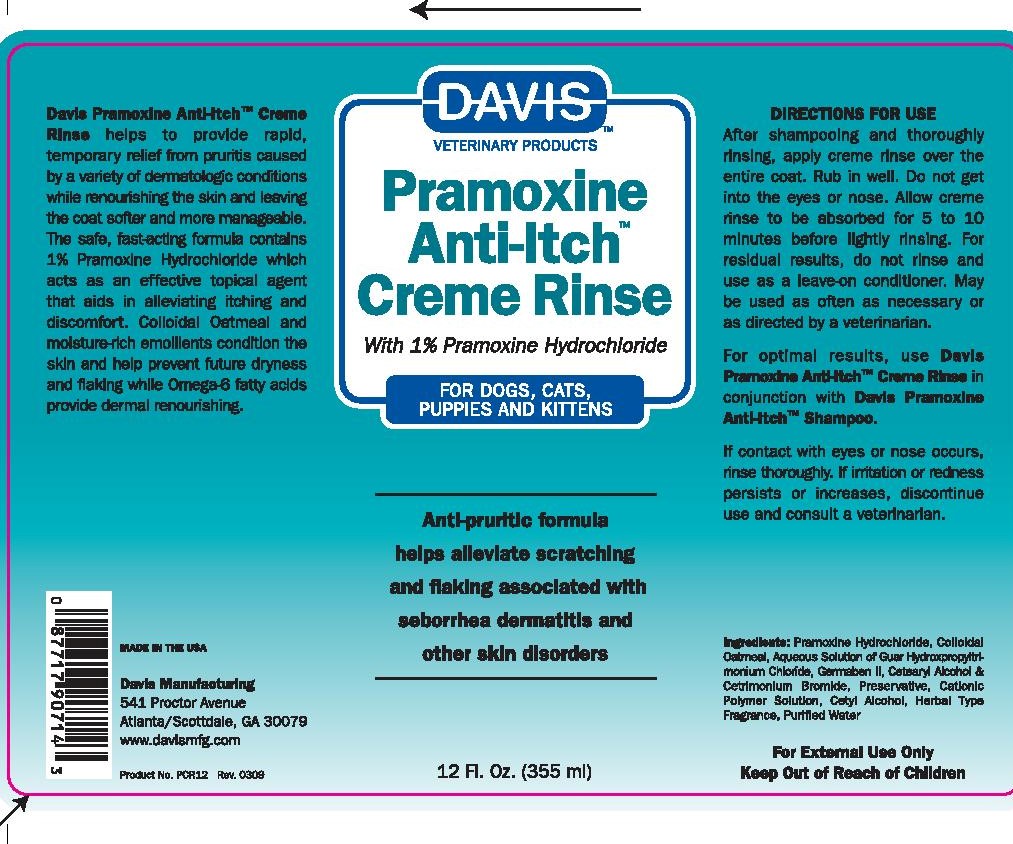 DRUG LABEL: Davis Pramoxine Anti-Itch
NDC: 62570-100 | Form: LOTION/SHAMPOO
Manufacturer: Davis Manufacturing and Packaging Inc
Category: animal | Type: OTC ANIMAL DRUG LABEL
Date: 20180427

ACTIVE INGREDIENTS: PRAMOXINE HYDROCHLORIDE 1 mg/1 g
INACTIVE INGREDIENTS: WATER; POLYQUATERNIUM-47 (METHACRYLAMIDOPROPYLTRIMETHYLAMMONIUM CHLORIDE-CO-METHYL ACRYLATE-CO-ACRYLIC ACID 45:10:45; 1200000 MW); CETRIMONIUM BROMIDE; CETOSTEARYL ALCOHOL; CETYL ALCOHOL; TROLAMINE; GUAR HYDROXYPROPYLTRIMONIUM CHLORIDE (1.7 SUBSTITUENTS PER SACCHARIDE); oatmeal; DIAZOLIDINYL UREA; FD&C YELLOW NO. 5

Pramoxine Anti-Itch Creme Rinse With 1% Pramoxine Hydrochloride

DESCRIPTION

Davis Pramoxine Anti-ItchTM Creme Rinse helps to provide rapid, temporary relief from pruitis caused by a variety of dermatologic conditions while renourishing the skin and leaving the coat more manageable. The safe, fast-acting formula contains 1% Pramoxine Hydrochloride which acts as an effective topical agent that aids in alleviating itching and discomfort. Colloidal Oatmeal and moisture-rich emollients condition and nourish the skin and help prevent future dryness and flaking.

Made in the USA

Manufactured by:

Davis Manufacturing

541 Proctor Avenue

Scottdale, GA 30079

www.davismfg.com

Active Ingredient: Pramoxine Hydrochloride 1.0%

INACTIVE INGREDIENT

Inactive Ingredients: Purified Water, Cetyl Alcohol, Cetearyl Alcohol & Cetrimonium Bromide, Modified Acrylic Polymer, Germaben II, Cationic Guar Gum, FD&C Yellow #5, Chocolate Dye

DIRECTIONS FOR USE

After shampooing and thoroughly rinsing, aplly creme rinse over the entire coat. Rub in Well. Do not get into eyes or nose. Allow creme rinse to be absorbed for 5 to 10 minutes before lightly rinsing. For residual results, do not rinse and use as a leave on conditioner. May be used as often as necessary or as directed by a veterinarian.

PRECAUTIONS

If contact with eyes or nose occurs, rinse thoroughly. If irritation or redness presists or increases, discontinue use and consult a veterinarian.

For External Use Only

Keep out of Reach

of Children and Pets

Gallon display panel

Davis Veterinary Products

Pramoxine

Anti-ItchTM

Creme Rinse

With 1% Pramoxine Hydrochloride

For Dogs, Cats, Puppies and Kittens

Anti-pruritic formula alleviates

scratching and flaking associated with

seborrhea dermititis and other skin disorders.

1 Gallon (3.785 Liters)

355 ml size

Davis Veterinary Products

Pramoxine

Anti-ItchTM

Creme Rinse

With 1% Pramoxine Hydrochloride

For Dogs, Cats, Puppies and Kittens

Anti-pruritic formula alleviates

scratching and flaking associated with

seborrhea dermititis and other skin disorders.

12 Fl. Oz. (355 ml)